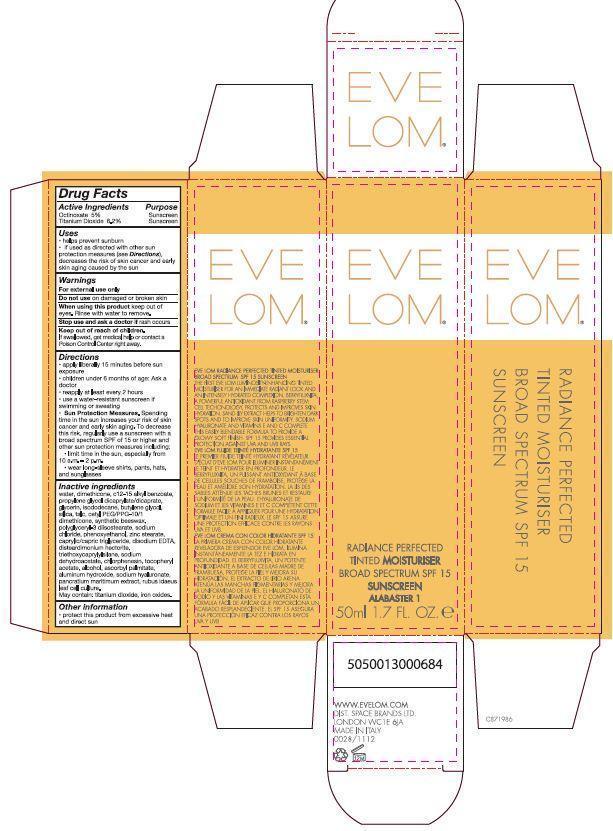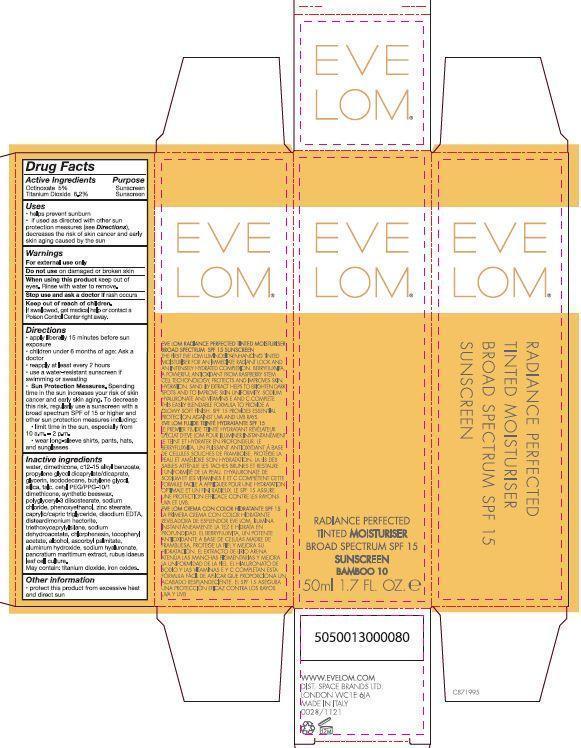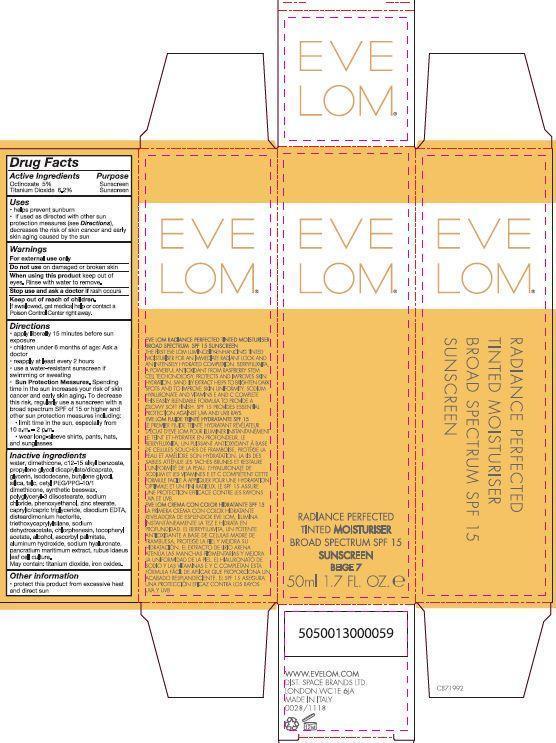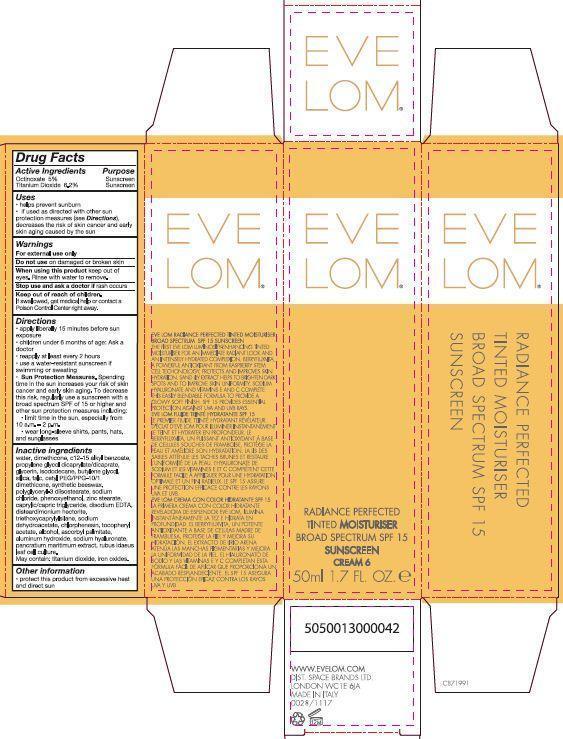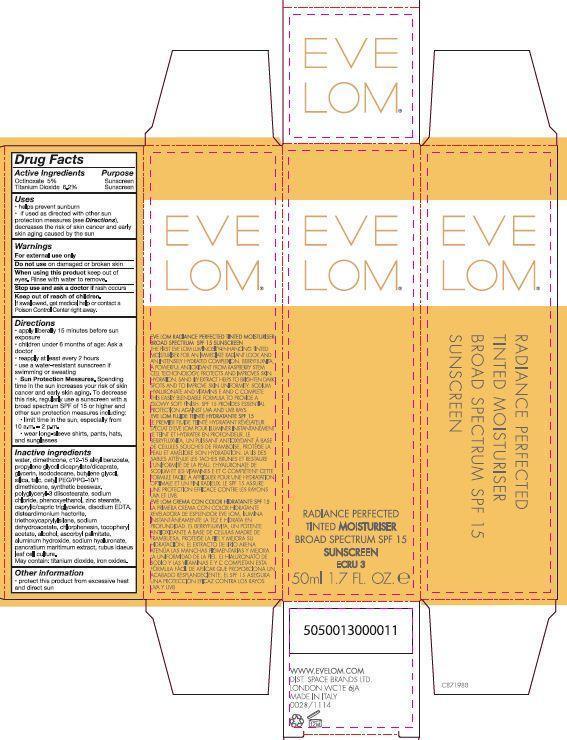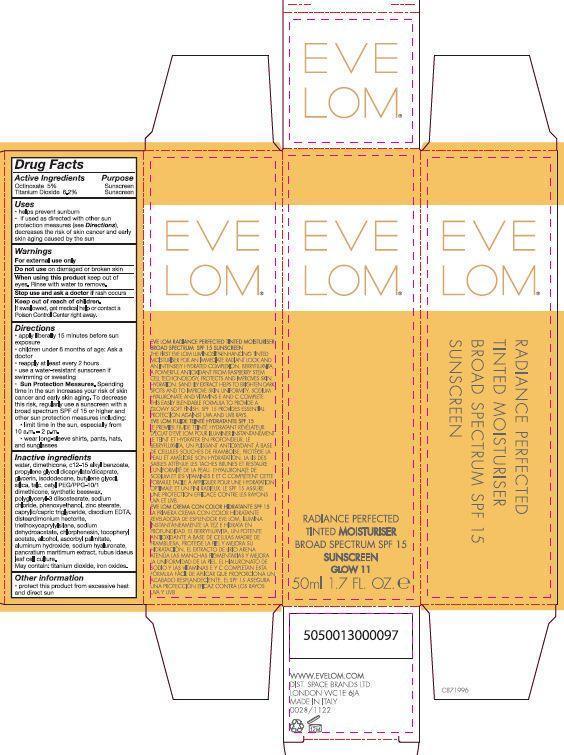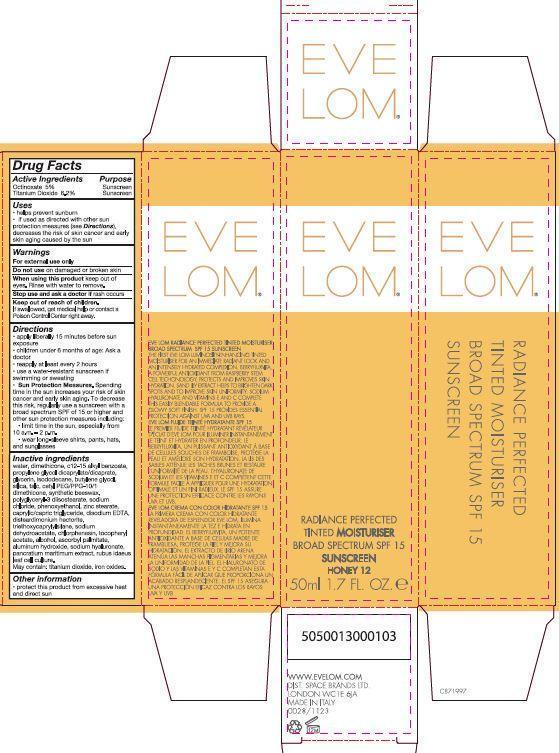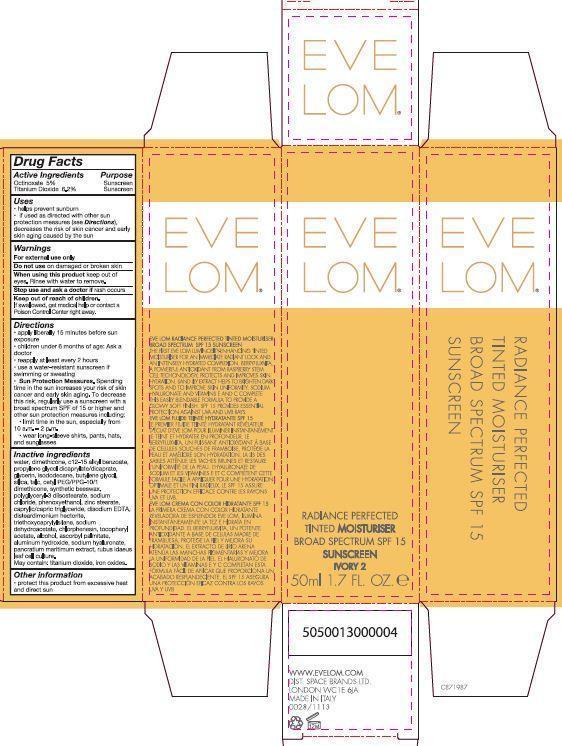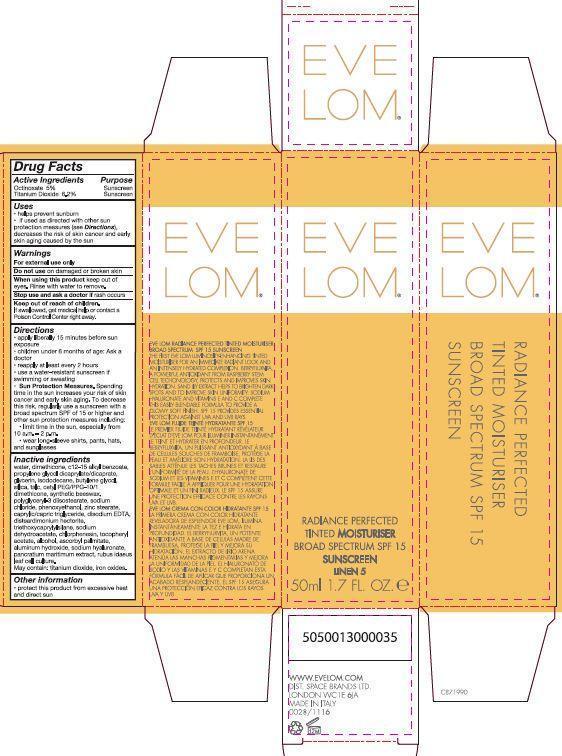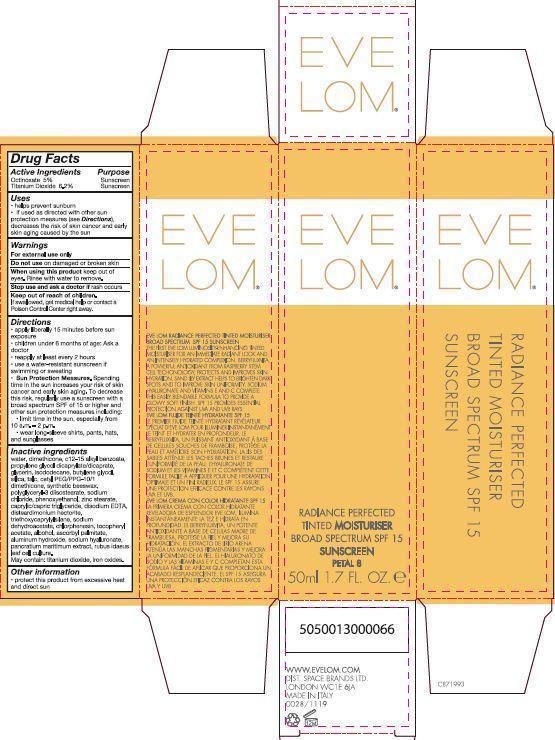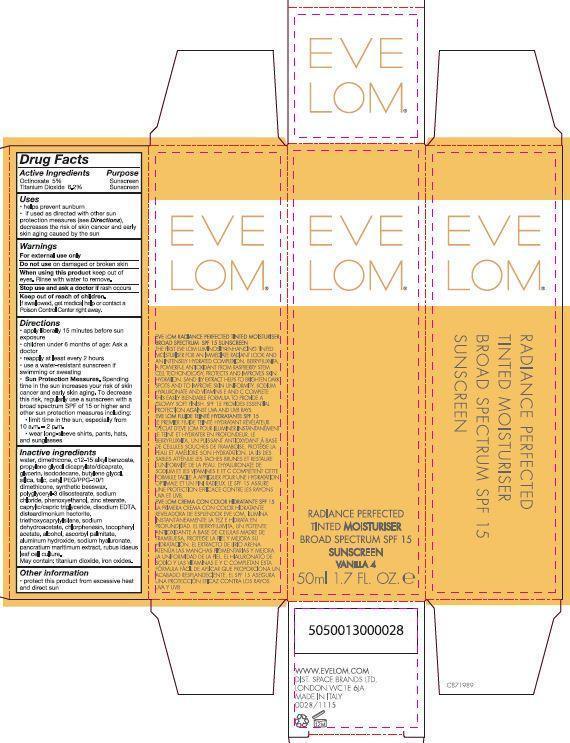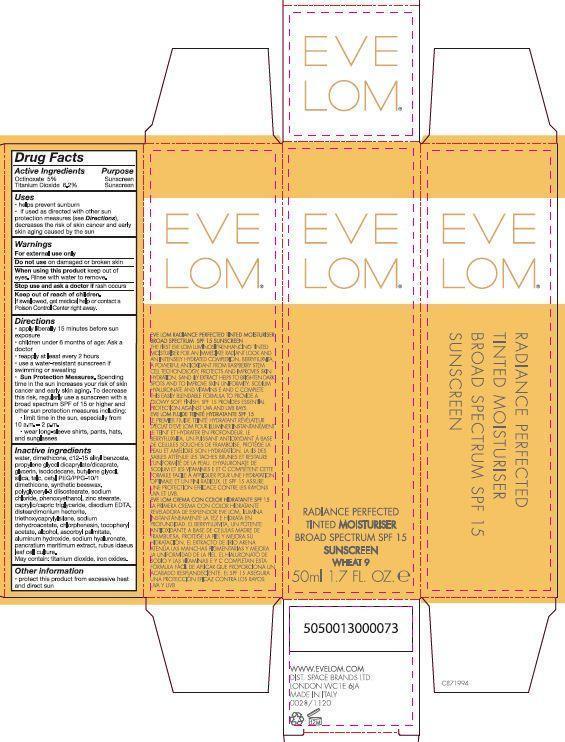 DRUG LABEL: Eve Lom Radiance Perfected Tinted Moisturiser Broad Spectrum SPF 15 Sunscreen
NDC: 61601-1112 | Form: CREAM
Manufacturer: Space Brands Limited
Category: otc | Type: HUMAN OTC DRUG LABEL
Date: 20140320

ACTIVE INGREDIENTS: TITANIUM DIOXIDE 3.1 g/50 mL; OCTINOXATE 2.5 g/50 mL
INACTIVE INGREDIENTS: WATER; DIMETHICONE; ALKYL (C12-15) BENZOATE; PROPYLENE GLYCOL DICAPRYLATE/DICAPRATE; GLYCERIN; ISODODECANE; BUTYLENE GLYCOL; SILICON DIOXIDE; TALC; CETYL PEG/PPG-10/1 DIMETHICONE (HLB 2); POLYGLYCERYL-3 DIISOSTEARATE; SODIUM CHLORIDE; FERRIC OXIDE YELLOW; PHENOXYETHANOL; ZINC STEARATE; MEDIUM-CHAIN TRIGLYCERIDES; EDETATE SODIUM; DISTEARDIMONIUM HECTORITE; TRIETHOXYCAPRYLYLSILANE; SODIUM DEHYDROACETATE; CHLORPHENESIN; .ALPHA.-TOCOPHEROL ACETATE; ALCOHOL; ALUMINUM HYDROXIDE; FERRIC OXIDE RED; ASCORBYL PALMITATE; FERROSOFERRIC OXIDE; HYALURONATE SODIUM

Eve Lom® Radiance Perfected Tinted Moisturiser Broad Spectrum SPF 15 Sunscreen

Drug Facts

ACTIVE INGREDIENT

Active Ingredients Purpose

Octinoxate 5% Sunscreen

Titanium Dioxide 6.2% Sunscreen

Uses

- helps prevent sunburn
- if used as directed with other sun protection measure (see Directions), decreases the risk of skin cancer and early skin aging caused by the sun

Warnings

For external use only

Do not use on damaged or broken skin

When using this product keep out of eyes. Rinse with water to remove.

Stop use and ask a doctor if rash occurs.

Keep out of reach of children. If swallowed, get medical help or contact a Poison Control Center right away.

Directions

- apply liberally 15 minutes before sun exposure
- children under 6 months of age: Ask a doctor
- reapply at least every 2 hours
- use a water-resistant sunscreen if swimming or sweating
- Sun Protection Measures. Spending time in the sun increases your risk of skin cancer and early skin aging. To decrease this risk, regularly use a sunscreen with a broad spectrum SPF of 15 or higher and other sun protection measures including:
  - limit time in the sun, especially from 10 a.m. – 2 p.m.
  - wear long-sleeve shirts, pants, hats, and sunglasses

INACTIVE INGREDIENT

water, dimethicone, c 12-15 alkly benzoate, propylene glycol dicaprylate/dicaprate, glycerin, isododecane, butylene glycol, silica, talc, cetyl PEG/PPG-10/1 dimethicone, synthetic beeswax, polyglyceryl-3 diisostearate, sodium chloride, phenoxyethanol, zinc stearate, caprylic/capric triglyceride, disodium EDTA, disteardimonium hectorite, triethoxycaprylylsilane, sodium dehydroacetate, chlorphenesin, tocopheryl acetate, alcohol, ascorbyl palmitate, aluminum hydroxide, sodium hyaluronate, pancratium maritimum extract, rubus idaeus leaf cell culture.

May contain: titanium dioxide, iron oxides.

Other information

- protect this product from excessive heat and direct sun

PRINCIPAL DISPLAY PANEL - 50 mL Tube Carton - Alabaster

EVE LOM®

RADIANCE PERFECTED

TINTED MOISTURISER

BROAD SPECTRUM SPF 15

SUNSCREEN

ALABASTER 1

50 ml 1.7 FL. OZ e

PRINCIPAL DISPLAY PANEL - 50 mL Tube Carton - Ivory

EVE LOM®

RADIANCE PERFECTED

TINTED MOISTURISER

BROAD SPECTRUM SPF 15

SUNSCREEN

IVORY 2

50 ml 1.7 FL. OZ e

PRINCIPAL DISPLAY PANEL - 50 mL Tube Carton - Ecru

EVE LOM®

RADIANCE PERFECTED

TINTED MOISTURISER

BROAD SPECTRUM SPF 15

SUNSCREEN

ECRU 3

50 ml 1.7 FL. OZ e

PRINCIPAL DISPLAY PANEL - 50 mL Tube Carton - Vanilla

EVE LOM®

RADIANCE PERFECTED

TINTED MOISTURISER

BROAD SPECTRUM SPF 15

SUNSCREEN

VANILLA 4

50 ml 1.7 FL. OZ e

PRINCIPAL DISPLAY PANEL - 50 mL Tube Carton - Linen

EVE LOM®

RADIANCE PERFECTED

TINTED MOISTURISER

BROAD SPECTRUM SPF 15

SUNSCREEN

LINEN 5

50 ml 1.7 FL. OZ e

PRINCIPAL DISPLAY PANEL - 50 mL Tube Carton - Cream

EVE LOM®

RADIANCE PERFECTED

TINTED MOISTURISER

BROAD SPECTRUM SPF 15

SUNSCREEN

CREAM 6

50 ml 1.7 FL. OZ e

PRINCIPAL DISPLAY PANEL - 50 mL Tube Carton - Beige

EVE LOM®

RADIANCE PERFECTED

TINTED MOISTURISER

BROAD SPECTRUM SPF 15

SUNSCREEN

BEIGE 7

50 ml 1.7 FL. OZ e

PRINCIPAL DISPLAY PANEL - 50 mL Tube Carton - Petal

EVE LOM®

RADIANCE PERFECTED

TINTED MOISTURISER

BROAD SPECTRUM SPF 15

SUNSCREEN

PETAL 8

50 ml 1.7 FL. OZ e

PRINCIPAL DISPLAY PANEL - 50 mL Tube Carton - Wheat

EVE LOM®

RADIANCE PERFECTED

TINTED MOISTURISER

BROAD SPECTRUM SPF 15

SUNSCREEN

WHEAT 9

50 ml 1.7 FL. OZ e

PRINCIPAL DISPLAY PANEL - 50 mL Tube Carton - Bamboo

EVE LOM®

RADIANCE PERFECTED

TINTED MOISTURISER

BROAD SPECTRUM SPF 15

SUNSCREEN

BAMBOO 10

50 ml 1.7 FL. OZ e

PRINCIPAL DISPLAY PANEL - 50 mL Tube Carton - Glow

EVE LOM®

RADIANCE PERFECTED

TINTED MOISTURISER

BROAD SPECTRUM SPF 15

SUNSCREEN

GLOW 11

50 ml 1.7 FL. OZ e

PRINCIPAL DISPLAY PANEL - 50 mL Tube Carton - Honey

EVE LOM®

RADIANCE PERFECTED

TINTED MOISTURISER

BROAD SPECTRUM SPF 15

SUNSCREEN

HONEY 12

50 ml 1.7 FL. OZ e